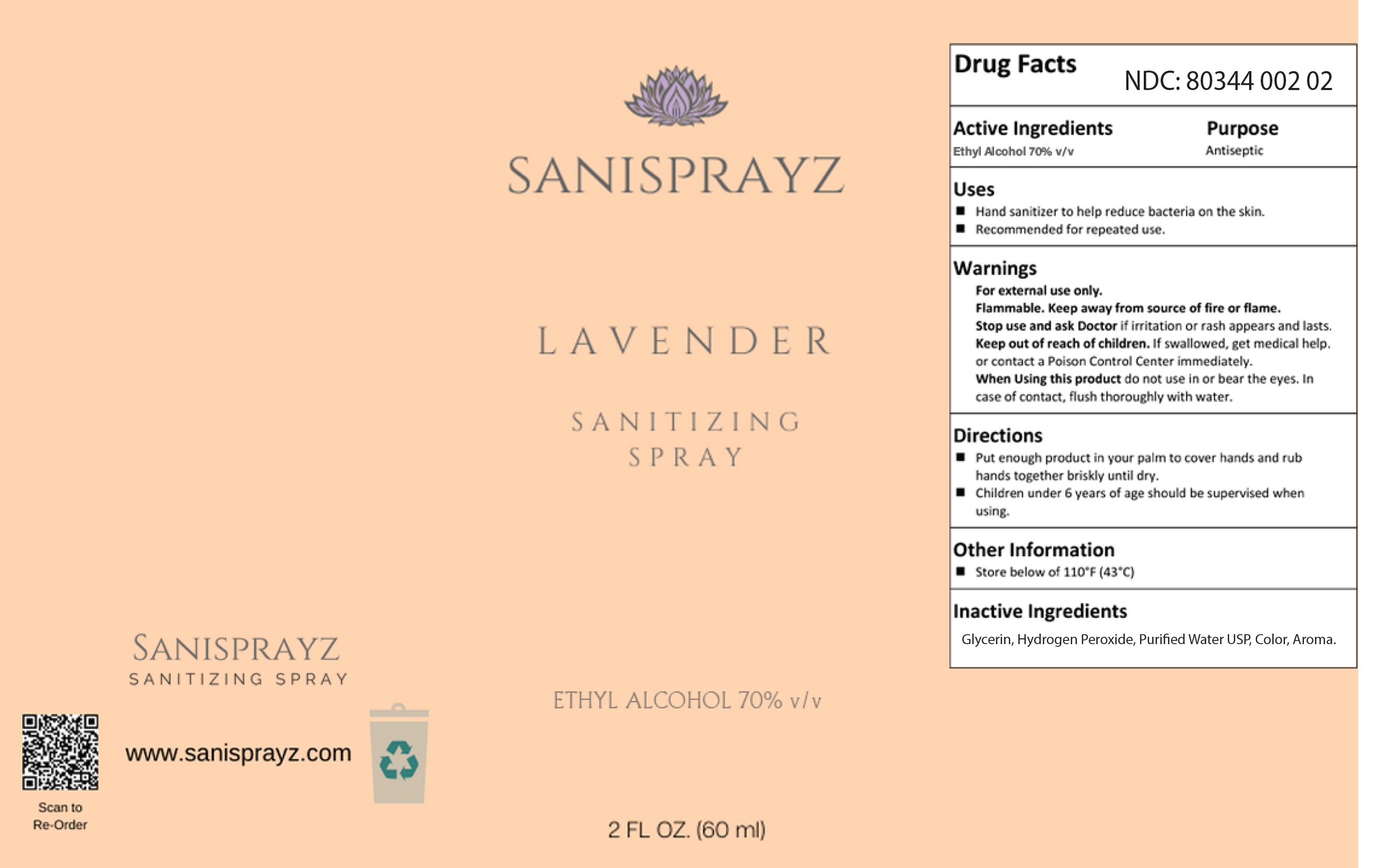 DRUG LABEL: Sanisprayz Lavender Sanitizing
NDC: 80344-002 | Form: SPRAY
Manufacturer: Birch Farms Inc.
Category: otc | Type: HUMAN OTC DRUG LABEL
Date: 20201008

ACTIVE INGREDIENTS: ALCOHOL 0.7 mL/1 mL
INACTIVE INGREDIENTS: GLYCERIN; HYDROGEN PEROXIDE; WATER

Sanisprayz Lavender Sanitizing Spray

Active Ingredients

Ethyl Alcohol 70%v/v

Purpose

Antiseptic

Uses

- Hand sanitizer to help reduce bacteria on the skin.
- Recommended for repeated use.

Warnings

For external use only.

Flammable. Keep away from source of fire or flame.

Stop use and ask a Doctor

if irritation or rash appears and lasts.

Keep out of reach of children.

If swallowed, get medical help. or contact a Poison Control Center immediately.

When Using this product

do not use in or near the eyes. In case of contact, flush thoroughly with water.

Directions

- Put enough product in your palm to cover hands and rub hands together briskly until dry.
- Children under 6 years of age should be supervised when using.

Other Information

- Store below of 110°F (43°C)

Inactive Ingredients

Glycerin, Hydrogen Peroxide, Purified Water USP, Color, Aroma.